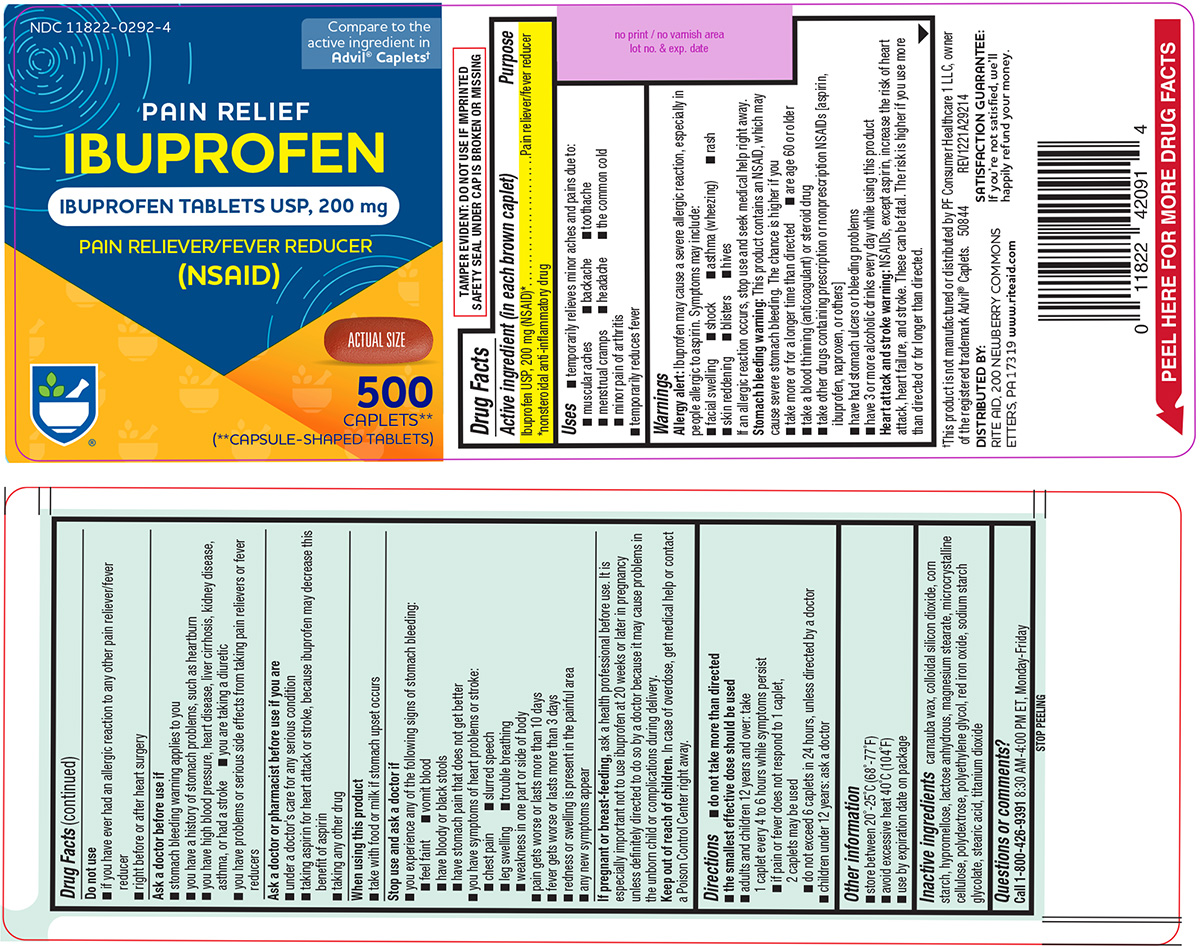 DRUG LABEL: Pain Relief Ibuprofen
NDC: 11822-0292 | Form: TABLET, FILM COATED
Manufacturer: Rite Aid Corporation
Category: otc | Type: HUMAN OTC DRUG LABEL
Date: 20260203

ACTIVE INGREDIENTS: IBUPROFEN 200 mg/1 1
INACTIVE INGREDIENTS: CARNAUBA WAX; SILICON DIOXIDE; STARCH, CORN; HYPROMELLOSE, UNSPECIFIED; ANHYDROUS LACTOSE; MAGNESIUM STEARATE; MICROCRYSTALLINE CELLULOSE; POLYDEXTROSE; POLYETHYLENE GLYCOL, UNSPECIFIED; FERRIC OXIDE RED; SODIUM STARCH GLYCOLATE TYPE A POTATO; STEARIC ACID; TITANIUM DIOXIDE

Rite Aid 44-292

Active ingredient (in each brown caplet)

Ibuprofen USP, 200 mg (NSAID)*
*nonsteroidal anti-inflammatory drug

Purpose

Pain reliever/fever reducer

Uses

- temporarily relieves minor aches and pains due to:
  - menstrual cramps
  - toothache
  - the common cold
  - backache
  - headache
  - muscular aches
  - minor pain of arthritis
- temporarily reduces fever

Warnings

Allergy alert: Ibuprofen may cause a severe allergic reaction, especially in people allergic to aspirin. Symptoms may include:

- skin reddening
- asthma (wheezing)
- rash
- facial swelling
- shock
- blisters
- hives

If an allergic reaction occurs, stop use and seek medical help right away.

Stomach bleeding warning: This product contains an NSAID, which may cause severe stomach bleeding. The chance is higher if you

- take more or for a longer time than directed
- take a blood thinning (anticoagulant) or steroid drug
- are age 60 or older
- take other drugs containing prescription or nonprescription NSAIDs [aspirin, ibuprofen, naproxen, or others]
- have had stomach ulcers or bleeding problems
- have 3 or more alcoholic drinks every day while using this product

Heart attack and stroke warning: NSAIDs, except aspirin, increase the risk of heart attack, heart failure, and stroke. These can be fatal. The risk is higher if you use more than directed or for longer than directed.

Do not use

- if you have ever had an allergic reaction to any other pain reliever/fever reducer
- right before or after heart surgery

Ask a doctor before use if

- you have a history of stomach problems, such as heartburn
- you are taking a diuretic
- you have high blood pressure, heart disease, liver cirrhosis, kidney disease, asthma, or had a stroke
- stomach bleeding warning applies to you
- you have problems or serious side effects from taking pain relievers or fever reducers

Ask a doctor or pharmacist before use if you are

- under a doctor's care for any serious condition
- taking aspirin for heart attack or stroke, because ibuprofen may decrease this benefit of aspirin
- taking any other drug

When using this product

- take with food or milk if stomach upset occurs

Stop use and ask a doctor if

- you experience any of the following signs of stomach bleeding:
  - feel faint
  - vomit blood
  - have bloody or black stools
  - have stomach pain that does not get better
- you have symptoms of heart problems or stroke:
  - chest pain
  - trouble breathing
  - leg swelling
  - slurred speech
  - weakness in one part or side of body
- pain gets worse or lasts more than 10 days
- fever gets worse or lasts more than 3 days
- redness or swelling is present in the painful area
- any new symptoms appear

If pregnant or breast-feeding,

ask a health professional before use. It is especially important not to use ibuprofen at 20 weeks or later in pregnancy unless definitely directed to do so by a doctor because it may cause problems in the unborn child or complications during delivery.

Keep out of reach of children.

In case of overdose, get medical help or contact a Poison Control Center right away.

Directions

- do not take more than directed
- the smallest effective dose should be used
- adults and children 12 years and over: take 1 caplet every 4 to 6 hours while symptoms persist
  - if pain or fever does not respond to 1 caplet, 2 caplets may be used
  - do not exceed 6 caplets in 24 hours, unless directed by a doctor
- children under 12 years: ask a doctor

Other information

- store between 20°-25°C (68°-77°F)
- avoid excessive heat 40°C (104°F)
- see end flap for expiration date and lot number

Inactive ingredients

carnauba wax, colloidal silicon dioxide, corn starch, hypromellose, lactose anhydrous, magnesium stearate, microcrystalline cellulose, polydextrose, polyethylene glycol, red iron oxide, sodium starch glycolate, stearic acid, titanium dioxide

Questions or comments?

Call 1-800-426-9391 8:30 AM-4:00 PM ET, Monday-Friday

Principal Display Panel

NDC 11822-0292-4

Compare to the
active ingredient in
Advil® Caplets†

PAIN RELIEF
IBUPROFEN
IBUPROFEN TABLETS USP, 200 mg

PAIN RELIEVER/FEVER REDUCER
(NSAID)

ACTUAL SIZE

500
CAPLETS**
(**CAPSULE-SHAPED TABLETS)

TAMPER EVIDENT: DO NOT USE IF IMPRINTED
SAFETY SEAL UNDER CAP IS BROKEN OR MISSING

†This product is not manufactured or distributed by PF
Consumer Healthcare 1 LLC, owner of the registered trademark
Advil® Caplets. 50844 REV1221A29214

DISTRIBUTED BY:
RITE AID, 200 NEWBERRY COMMONS
ETTERS, PA 17319 www.riteaid.com

SATISFACTION GUARANTEE:
If you’re not satisfied, we’ll
happily refund your money.

Rite Aid 44-292